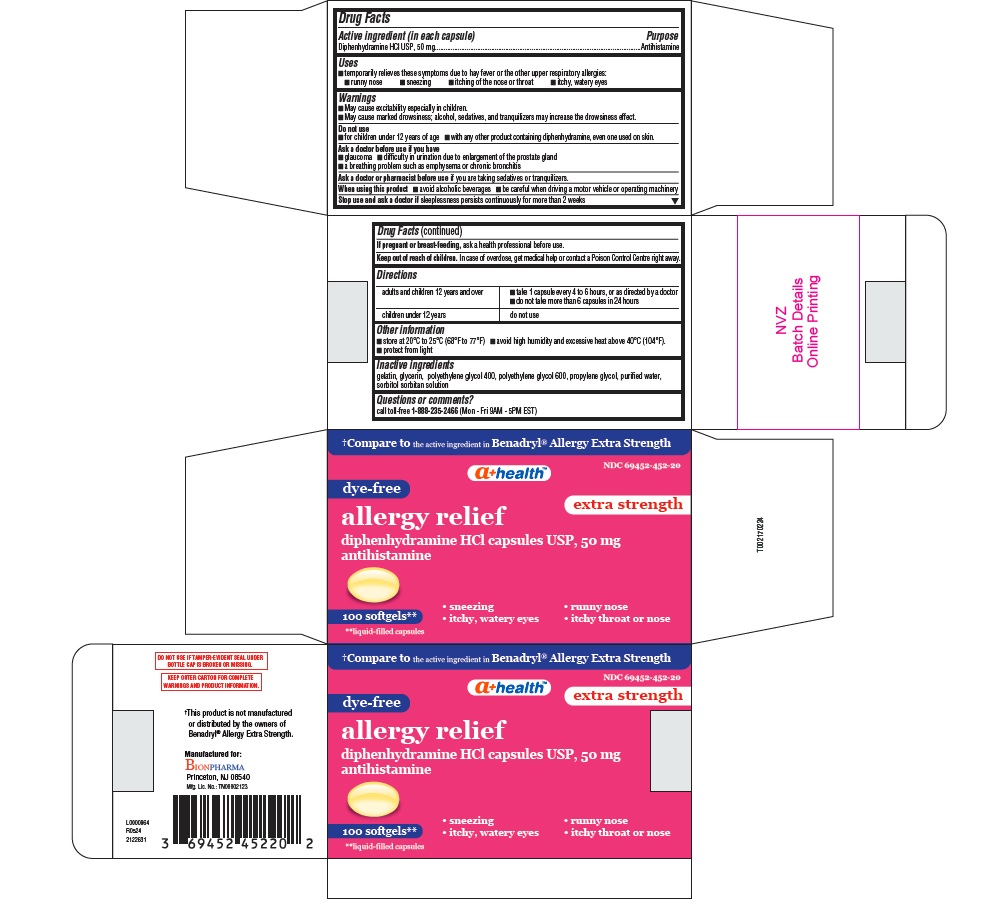 DRUG LABEL: Allergy Relief
NDC: 69452-452 | Form: CAPSULE, LIQUID FILLED
Manufacturer: BIONPHARMA INC.
Category: otc | Type: HUMAN OTC DRUG LABEL
Date: 20260227

ACTIVE INGREDIENTS: DIPHENHYDRAMINE HYDROCHLORIDE 50 mg/1 1
INACTIVE INGREDIENTS: POLYETHYLENE GLYCOL 600; SORBITAN; GELATIN; POLYETHYLENE GLYCOL 400; WATER; GLYCERIN; PROPYLENE GLYCOL; SORBITOL

Diphenhydramine HCl 50mg, A+ Health, allergy relief

Active ingredient (in each capsule)

Diphenhydramine HCl 50 mg

Purpose

Antihistamine

Uses

■ temporarily relieves these symptoms due to hay fever or the other upper respiratory allergies:
■ runny nose ■ sneezing ■ itching of the nose or throat ■ itchy, watery eyes

Warnings

■ May cause excitability especially in children.
■ May cause marked drowsiness; alcohol, sedatives, and tranquilizers may increase the drowsiness effect.

Do not use

■ for children under 12 years of age ■ with any other product containing diphenhydramine, even one used on skin.

Ask a doctor before use if you have

■ glaucoma ■ difficulty in urination due to enlargement of the prostate gland
■ a breathing problem such as emphysema or chronic bronchitis

Ask a doctor or pharmacist before use

if you are taking sedatives or tranquilizers.

When using this product

■ avoid alcoholic beverages ■ be careful when driving a motor vehicle or operating machinery

Stop use and ask a doctor if

sleeplessness persists continuously for more than 2 weeks

If pregnant or breast- feeding,

ask a health professional before use.

Keep out of reach of children.

In case of overdose, get medical help or contact a Poison Control Centre right away.

Directions

adults and children 12 years and over | ■ take 1 capsule every 4 to 6 hours, or as directed by a doctor ■ do not take more than 6 capsules in 24 hours
children under 12 years | do not use

Other information

■ store at 20°C to 25°C (68°F to 77°F) ■ avoid high humidity and excessive heat above 40°C (104°F).
■ protect from light

Inactive ingredients

gelatin, glycerin, polyethylene glycol 400, polyethylene glycol 600, propylene glycol, purified water, sorbitol sorbitan solution

Questions or comments?

call toll-free 1-888-235-2466 (Mon - Fri 9AM - 5PM EST)

DO NOT USE IF TAMPER-EVIDENT SEAL UNDER BOTTLE CAP IMPRINTED WITH “SEALED for YOUR PROTECTION” IS BROKEN OR MISSING.

KEEP OUTER CARTON FOR COMPLETE WARNINGS AND PRODUCT INFORMATION.

†This product is not manufactured or distributed by the owners of Benadryl® Allergy Extra Strength.

Manufactured for:

Bionpharma

Princeton, NJ 08540

Mfg. Lic. No.: TN00002123

L0000864
R0524
2122631

100's count

†Compare to the active ingredient in Benadryl® Allergy Extra Strength

NDC 69452-452-20

a+ healthTM

dye-free

extra strength

allergy relief

diphenhydramine HCl capsules USP, 50 mg

antihistamine

• sneezing • runny nose
• itchy, watery eyes • itchy throat or nose

100 softgels **

**liquid-filled capsules